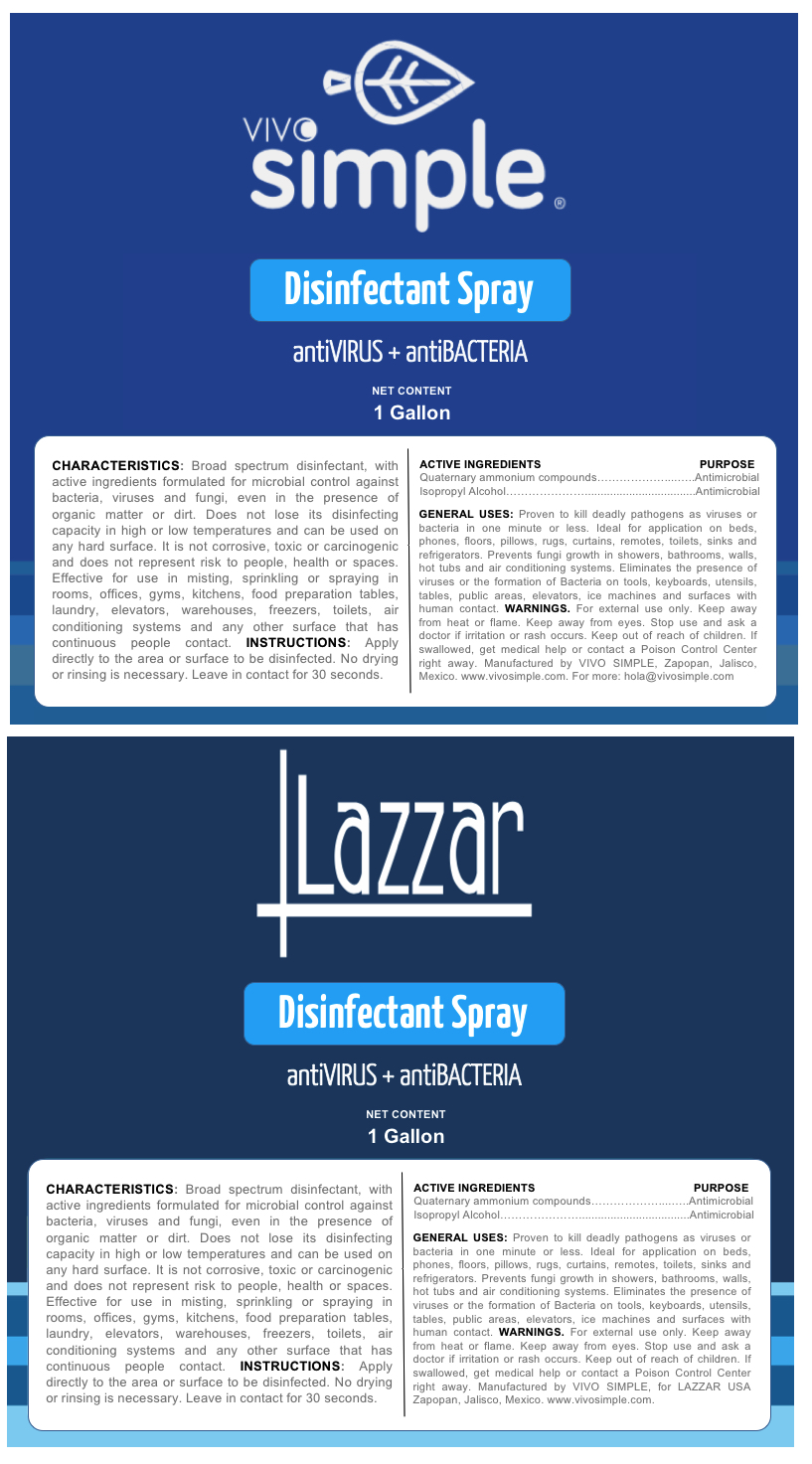 DRUG LABEL: VIVO SIMPLE
NDC: 79452-8000 | Form: SPRAY
Manufacturer: Cuellar Rosas, Juan Alberto
Category: otc | Type: HUMAN OTC DRUG LABEL
Date: 20200702

ACTIVE INGREDIENTS: ISOPROPYL ALCOHOL 0.2 mL/1 mL; N-ALKYL ETHYLBENZYL DIMETHYL AMMONIUM CHLORIDE (C12-C14) 0.02 mg/1 mL
INACTIVE INGREDIENTS: WATER 0.78 mL/1 mL

VIVO SIMPLE DISINFECTANT SPRAY

DOSAGE AND ADMINSTRATION

APPLY DIRECTLY TO THE AREA OR SURFACE TO BE DISINFECTED

INACTIVE INGREDIENTS

INACTIVE INGREDIENTS WATER

ACTIVE INGREDIENTS

ALKYL DIMETHYL ETHYLBENZYL AMMONIUM CHLORIDE

N-ALKYL DIMETHYL BENZYL AMMONIUM CHLORIDE

ISOPROPYL ALCOHOL

INDICATIONS

APPLY DIRECTLY TO THE AREA OR SURGACE TO BE DISINFECTED. NO DRYING OR RINSING IS NECESSARY. LEAVE IN CONTACT FOR 30 SECONDS.

KEEP OUT OF REACH OF CHILDREN

WARNINGS SECTIONS

Warnings

For external use only. Flammable. Keep away from heat or flame

WARNINGS AND PRECAUTIONS

When using this product keep out of eyes, ears, and mouth. In case of contact with eyes, rinse eyes thoroughly with water.

STOP USE

STOP USE AND ASK A DOCTOR IF IRRITATION OR RASH OCCURS.

PURPOSE

PURPOSE ANTIMICROBIAL